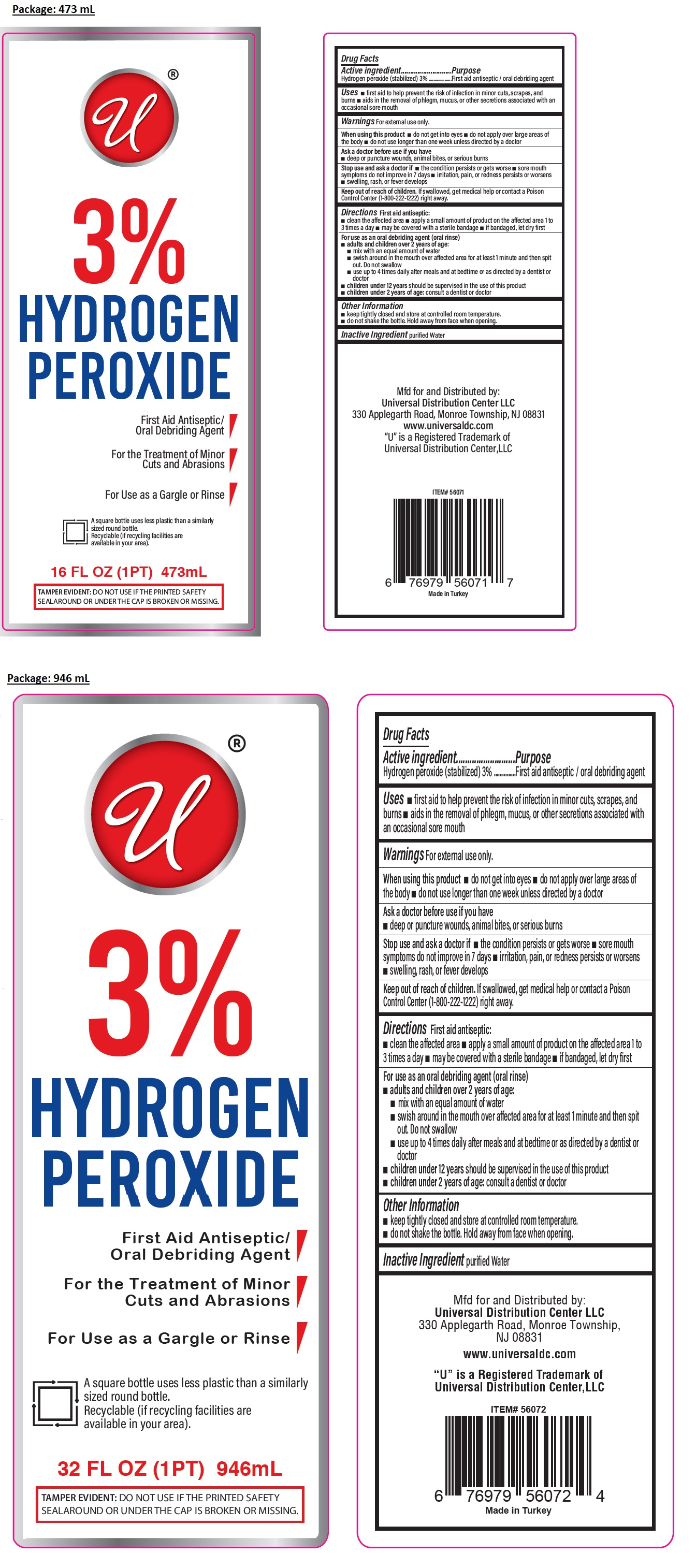 DRUG LABEL: 3% HYDROGEN PEROXIDE
NDC: 52000-433 | Form: SOLUTION
Manufacturer: Universal Distribution Center LLC
Category: otc | Type: HUMAN OTC DRUG LABEL
Date: 20251215

ACTIVE INGREDIENTS: HYDROGEN PEROXIDE 3 mL/100 mL
INACTIVE INGREDIENTS: WATER

3% HYDROGEN PEROXIDE

Active ingredient

Hydrogen peroxide (stabilized) 3%

Purpose

First aid antiseptic / oral debriding agent

Uses

• first aid to help prevent the risk of infection in minor cuts, scrapes, and burns • aids in the removal of phlegm, mucus, or other secretions associated with an occasional sore mouth

Warnings

For external use only.

When using this product • do not get into eyes • do not apply over large areas of the body • do not use longer than one week unless directed by a doctor

Ask a doctor before use if you have
• deep or puncture wounds, animal bites, or serious burns

Stop use and ask a doctor if • the condition persists or gets worse • sore mouth symptoms do not improve in 7 days • irritation, pain, or redness persists or worsens • swelling, rash, or fever develops

Keep out of reach of children. If swallowed, get medical help or contact a Poison Control Center (1-800-222-1222) right away.

Directions

First aid antiseptic:
• clean the affected area • apply a small amount of product on the affected area 1 to 3 times a day • may be covered with a sterile bandage • if bandaged, let dry first

For use as an oral debriding agent (oral rinse)
• adults and children over 2 years of age:
• mix with an equal amount of water
• swish around in the mouth over affected area for at least 1 minute and then spit out. Do not swallow
• use up to 4 times daily after meals and at bedtime or as directed by a dentist or doctor
• children under 12 years should be supervised in the use of this product
• children under 2 years of age: consult a dentist or doctor

Other information

• keep tightly closed and store at controlled room temperature.
• do not shake the bottle. Hold away from face when opening.

Inactive ingredient

purified Water

For the Treatment of Minor Cuts and Abrasions

For Use as a Gargle or Rinse

TAMPER EVIDENT: DO NOT USE IF THE PRINTED SAFETY SEAL AROUND OR UNDER THE CAP IS BROKEN OR MISSING.

Mfd for and Distributed by:
Universal Distribution Center LLC
330 Applegarth Road, Monroe Township,
NJ 08831

www.universaldc.com

“U” is a Registered Trademark of
Universal Distribution Center, LLC

Made in Turkey